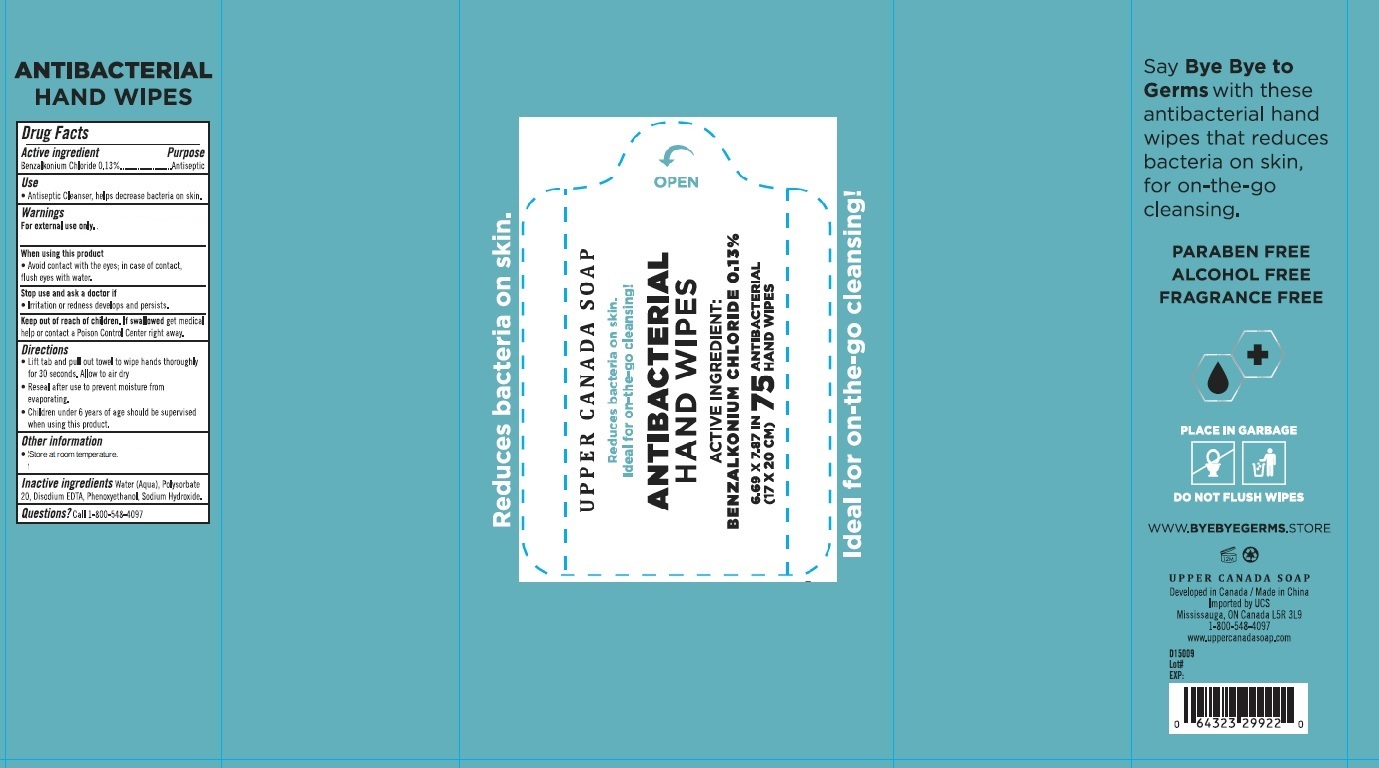 DRUG LABEL: Bye Bye Germs Antibacterial Wipes
NDC: 75109-002 | Form: CLOTH
Manufacturer: Kangna (Zhejiang) Medical Supplies Co., Ltd.
Category: otc | Type: HUMAN OTC DRUG LABEL
Date: 20201005

ACTIVE INGREDIENTS: BENZALKONIUM CHLORIDE 0.13 1/1 1
INACTIVE INGREDIENTS: WATER; POLYSORBATE 20; EDETATE DISODIUM ANHYDROUS; PHENOXYETHANOL; SODIUM HYDROXIDE

Drug Facts

Active ingredient

Benzalkonium Chloride 0.13%

Purpose

Antiseptic

Use

Antiseptic cleanser, helps decrease bacteria on skin.

Warnings

For external use only.

When using this product

Avoid contact with the eyes; in case of contact, flush eyes with water.

Stop use and ask a doctor if

irritation or redness develops and persists

Keep out of reach of children.

If injested, get medical help or contact a Poison Control Center right away

Directions

- Lift tab and pull out towel to wipe hands thoroughly for 30 seconds. Allow to air dry.
- Reseal after use to prevent moisture from evaporating.
- Children under 6 years of age should be supervised when using this product.

Other information

Store at room temperature.

Inactive ingredients

Water (Aqua), Polysorbate 20, Disodium EDTA, Phenoxyethanol, Sodium Hydroxide.

Questions?

Call 1-800-548-4097